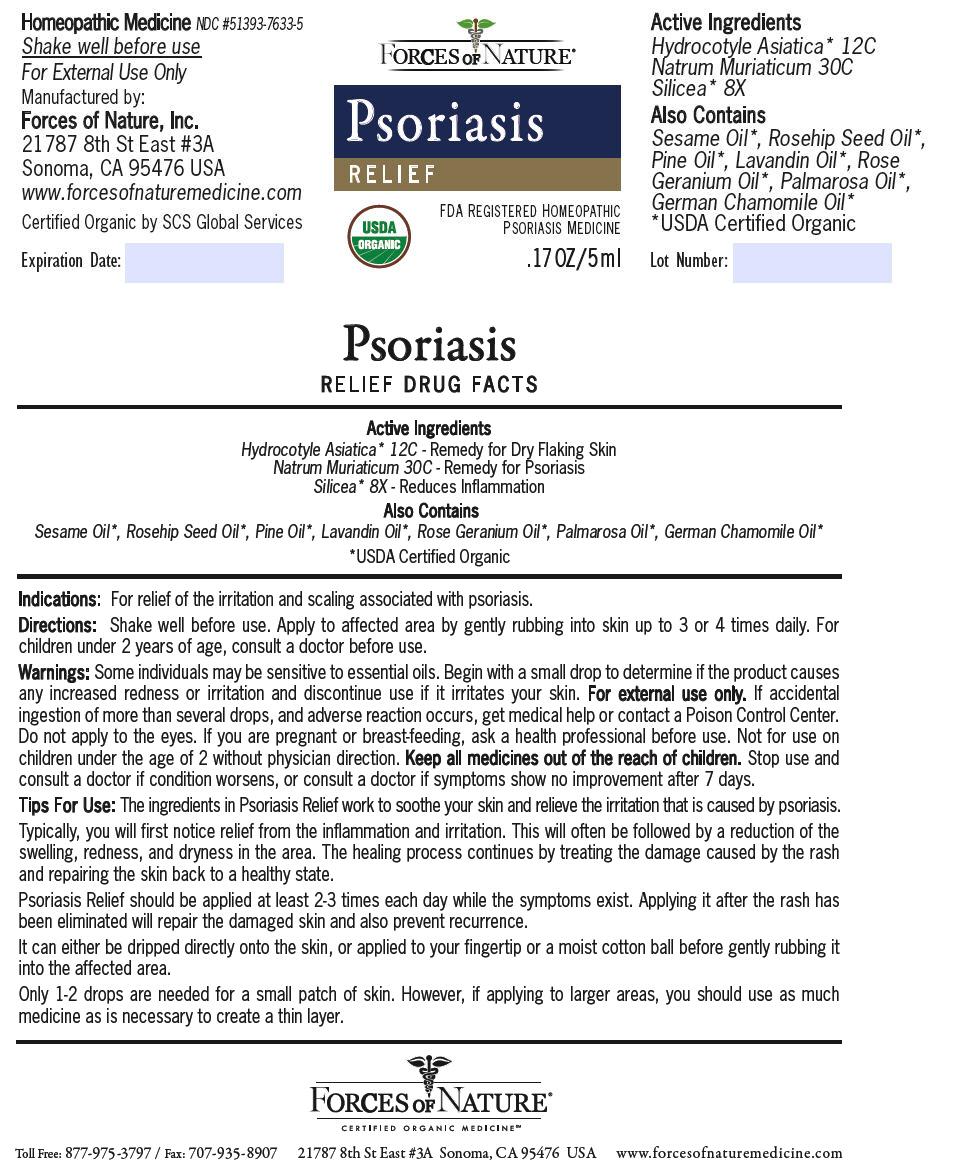 DRUG LABEL: Psoriasis Control
NDC: 51393-7633 | Form: SOLUTION/ DROPS
Manufacturer: Forces of Nature
Category: homeopathic | Type: HUMAN OTC DRUG LABEL
Date: 20200428

ACTIVE INGREDIENTS: Centella Asiatica 12 [hp_C]/1000 mL; Sodium Chloride 30 [hp_X]/1000 mL; Silicon Dioxide 8 [hp_X]/1000 mL
INACTIVE INGREDIENTS: Pine Needle Oil (Pinus Sylvestris); Lavandin Oil; Geranium Oil, Algerian Type; Chamomile Flower Oil; Palmarosa Oil; Rosa Moschata Oil; Sesame Oil

Psoriasis Control

DRUG FACTS

ACTIVE INGREDIENT

PURPOSE

Active Ingredients

Hydrocotyle Asiatica [USDA Certified Organic] 12C - Remedy for Dry Flaking Skin

Natrum Muriaticum 30C - Remedy for Psoriasis

Silicea 8X - Reduces Inflammation

Also Contains

Sesame Oil, Rosehip Seed Oil, Pine Oil, Lavandin Oil, Rose Geranium Oil, Palmarosa Oil, German Chamomile Oil

Indications

For relief of the irritation and scaling associated with psoriasis.

Directions

Shake well before use. Apply to affected area by gently rubbing into skin up to 3 or 4 times daily. For children under 2 years of age, consult a doctor before use.

Warnings

Some individuals may be sensitive to essential oils. Begin with a small drop to determine if the product causes any increased redness or irritation and discontinue use if it irritates your skin. For external use only. If accidental ingestion of more than several drops, and adverse reaction occurs, get medical help or contact a Poison Control Center. Do not apply to the eyes. If you are pregnant or breast-feeding, ask a health professional before use. Not for use on children under the age of 2 without physician direction.

KEEP OUT OF REACH OF CHILDREN

Keep all medicines out of the reach of children.

Stop use and consult a doctor if condition worsens, or consult a doctor if symptoms show no improvement after 7 days.

Tips For Use

The ingredients in Psoriasis Relief work to soothe your skin and relieve the irritation that is caused by psoriasis.

Typically, you will first notice relief from the inflammation and irritation. This will often be followed by a reduction of the swelling, redness, and dryness in the area. The healing process continues by treating the damage caused by the rash and repairing the skin back to a healthy state.

Psoriasis Relief should be applied at least 2-3 times each day while the symptoms exist. Applying it after the rash has been eliminated will repair the damaged skin and also prevent recurrence.

It can either be dripped directly onto the skin, or applied to your fingertip or a moist cotton ball before gently rubbing it into the affected area.

Only 1-2 drops are needed for a small patch of skin. However, if applying to larger areas, you should use as much medicine as is necessary to create a thin layer.

Manufactured by:
Forces of Nature, Inc.
21787 8th St East #3A
Sonoma, CA 95476 USA

PRINCIPAL DISPLAY PANEL - 5 ml Bottle Label

FORCES OF NATURE®

Psoriasis
RELIEF

FDA REGISTERED HOMEOPATHIC
PSORIASIS MEDICINE

USDA
ORGANIC

.17 OZ/5 ml